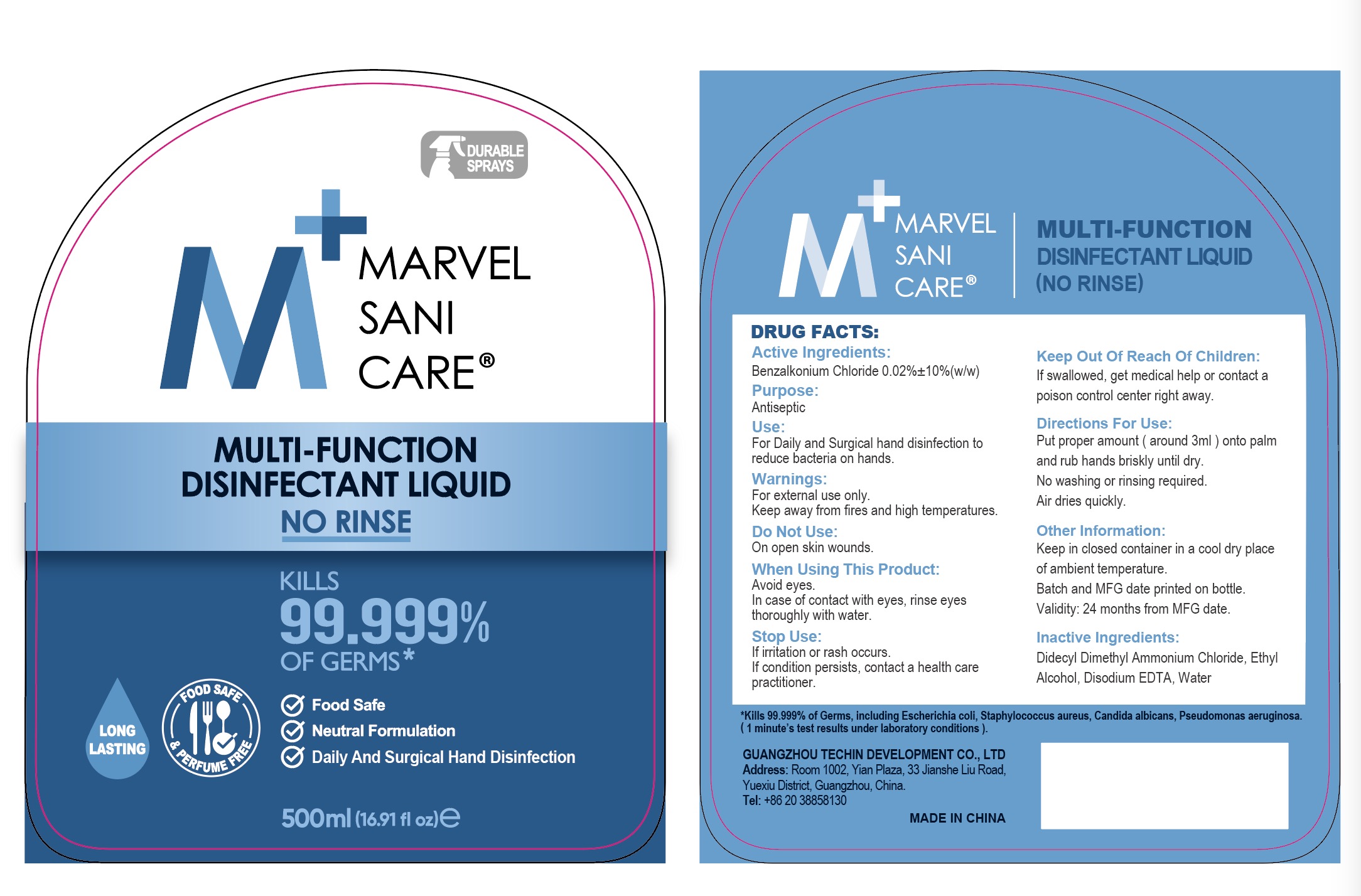 DRUG LABEL: M MARVEL SANI CARE Multi Function Disinfectant Liquid No Rinse
NDC: 80107-003 | Form: SPRAY
Manufacturer: GUANGZHOU TECHIN DEVELOPMENT CO., LTD
Category: otc | Type: HUMAN OTC DRUG LABEL
Date: 20220218

ACTIVE INGREDIENTS: BENZALKONIUM CHLORIDE 0.02 g/100 mL
INACTIVE INGREDIENTS: WATER; ALCOHOL; DISODIUM HEDTA

80107-003

Active Ingredient

Benzalkonium Chloride 0.02%

Purpose

Antiseptic

Use

For Daily and Surgical hand disinfection to reduce bacteria on hands

Warnings

For external use only.
Keep away from fires and high temperatures.

Do Not Use: On open skin wounds.

When using this product: Avoid eyes.
In case of contact with eyes, rinse eyes thoroughly with water.

Stop use If irritation or rash occurs. If condition persists, contact a health care practitioner.

Keep out of reach of children. If swallowed, get medical help or contact a Poison Control Center right away.

Directions

- Put proper amount (around 3ml) onto palm and rub hands briskly until dry.
- No washing or rinsing required. Air dries quickly.

Other information

Keep in closed container in a cool dry place of ambient temperature.
Batch and MFG date printed on bottle.
Validity: 24 months from MFG date.
MADE IN CHINA

Inactive ingredients

Didecyl Dimethyl Ammonium Chloride, Ethyl Alcohol, Disodium EDTA, Water